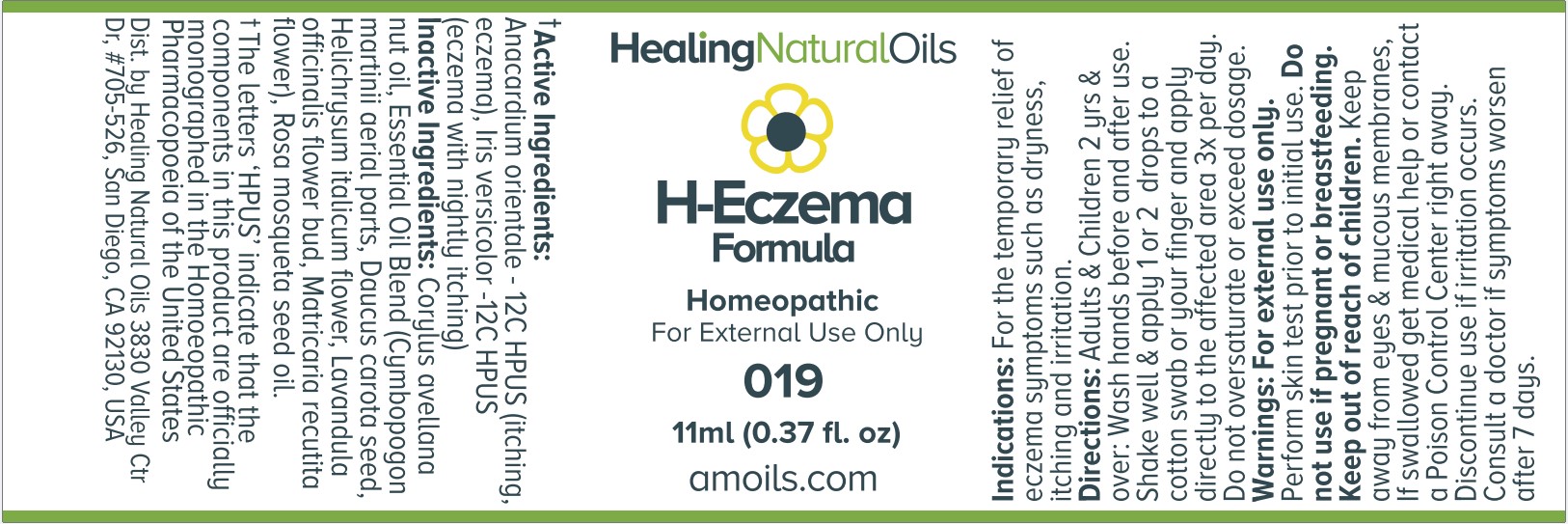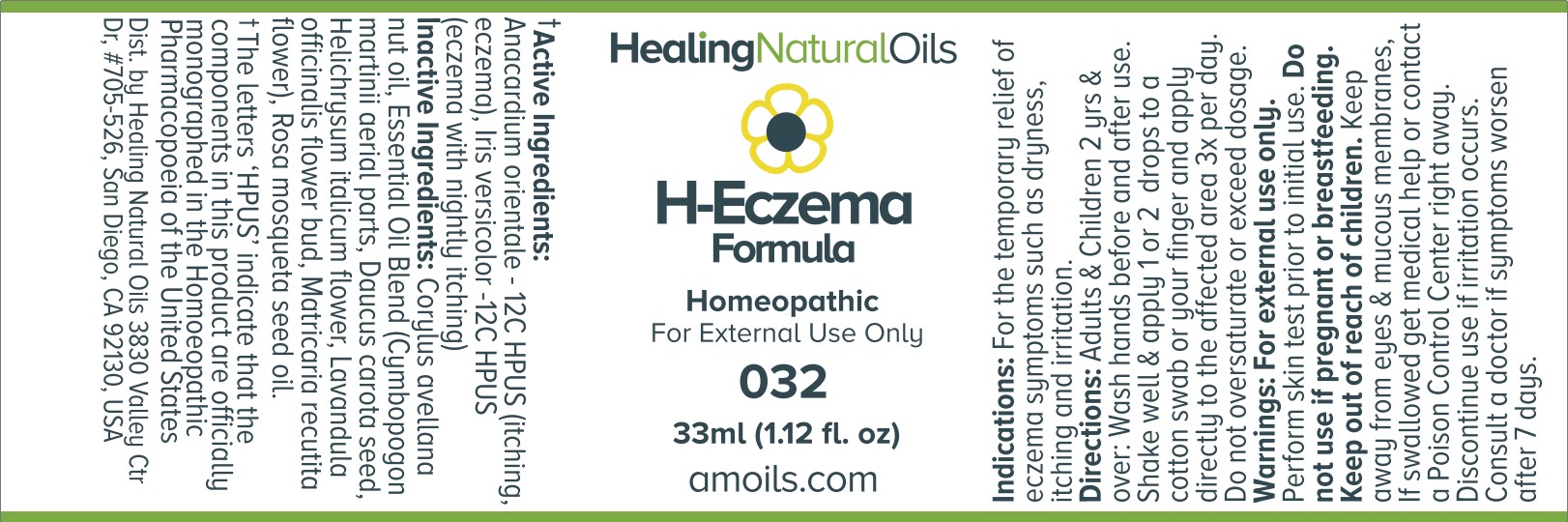 DRUG LABEL: H- Eczema Formula
NDC: 61077-019 | Form: OIL
Manufacturer: Healing Natural Oils
Category: homeopathic | Type: HUMAN OTC DRUG LABEL
Date: 20250527

ACTIVE INGREDIENTS: SEMECARPUS ANACARDIUM JUICE 12 [hp_C]/11 mL; IRIS VERSICOLOR ROOT 12 [hp_C]/11 mL
INACTIVE INGREDIENTS: CYMBOPOGON MARTINI TOP; LAVANDULA ANGUSTIFOLIA FLOWER; DAUCUS CAROTA SUBSP. SATIVUS SEED; CHAMOMILE; HELICHRYSUM ITALICUM FLOWER; EUROPEAN HAZELNUT OIL; ROSA MOSCHATA SEED OIL

H-Eczema Formula

Active Ingredients:

Anacardium orientale-12C HPUS
Iris versicolor-12C HPUS

Purpose

Anacardium orientale - 12C HPUS (itching, eczema),
Iris versicolor-12C HPUS (eczema with nightly itching)
The letters ‘HPUS’ indicate that the components in this product are officially
monographed in the Homoeopathic Pharmacopoeia of the United States

Indications:

For the temporary relief of eczema symptoms such as dryness, itching and irritation.

Directions:

Adults and Children 2 yrs and over: Wash hands before and after use.
Shake well and apply 1 or 2 drops to a cotton swab or your finger and apply directly to the affected area 3x per day.
Do not oversaturate or exceed dosage.

Warnings:

For external use only.

Perform skin test prior to initial use.

PREGNANCY OR BREAST FEEDING

If pregnant or breastfeeding consult a doctor before use.

Keep out of reach of children.

OTHER SAFETY INFORMATION

Keep away from eyes and mucous membranes. If swallowed get medical help
or contact a Poison Control Center right away.

Discontinue use if irritation occurs.

ASK DOCTOR

Consult a doctor if symptoms worsen after 7 days.

Inactive Ingredients:

Corylus avellana nut oil, Essential Oil Blend (Cymbopogon martinii aerial parts, Daucus carota seed, Helichrysum italicum flower,
Lavandula officinalis flower bud, Matricaria recutita flower), Rosa Mosqueta seed oil.

DESCRIPTION

Dist. by Healing Natural Oils 3830 Valley Ctr Dr, #705-526, San Diego, CA 92130, USA

PACKAGE LABEL

Healing Natural Oils

H-Eczema

Formula

Homeopathic

For External Use Only

019

11ml (0.37 fl. oz)

amoils.com